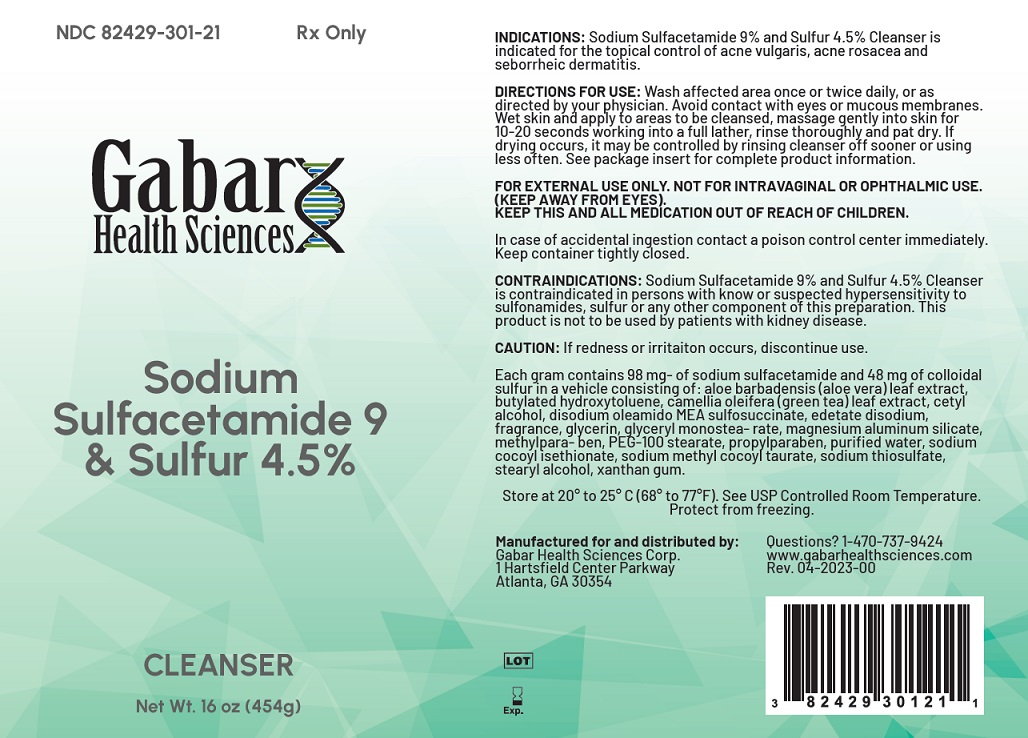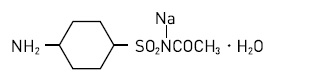 DRUG LABEL: Sodium Sulfacetamide 9% and Sulfur 4.5% Wash
NDC: 82429-301 | Form: RINSE
Manufacturer: Gabar Health Sciences Corp.
Category: prescription | Type: HUMAN PRESCRIPTION DRUG LABEL
Date: 20231021

ACTIVE INGREDIENTS: SULFACETAMIDE SODIUM 10 mg/1 g; SULFUR 5 mg/1 g
INACTIVE INGREDIENTS: ALOE VERA LEAF; BUTYLATED HYDROXYTOLUENE; CETYL ALCOHOL; EDETATE DISODIUM; DISODIUM OLEAMIDO MEA-SULFOSUCCINATE; GLYCERIN; GLYCERYL MONOSTEARATE; PEG-100 STEARATE; GREEN TEA LEAF; MAGNESIUM ALUMINUM SILICATE; METHYLPARABEN; PROPYLPARABEN; WATER; SODIUM COCOYL ISETHIONATE; SODIUM METHYL COCOYL TAURATE; SODIUM THIOSULFATE; STEARYL ALCOHOL; XANTHAN GUM

Sodium Sulfacetamide 9% and Sulfur 4.5% Wash

Rx Only

DESCRIPTION

Sodium Sulfacetamide is a sulfonamide with antibacterial with antibacterial activity while sulfur acts as a keratolytic agent. Chemically, Sodium Sulfacetamide is N-[(4-aminophenyl) sulfony]-acetamide, monosodium salt, monohydrate. The structural formula is:

Each mL of Sodium Sulfacetamide 9% & Sulfur 4.5% wash contains 90 mg of sodium sulfacetamide and 45 mg of sulfur in a formulation consisting of: aloe vera, fragrance, butylated hydroxytoluene, cetyl alcohol, disodium EDTA, disodium oleamido MEA sulfosuccinate, glyceryl stearate (and) PEG-100 stearate, green tea extract, magnesium aluminum silicate, methylparaben, propylparaben, purified water, sodium cocoyl isethionate, sodium methyl cocoyl tau rate, sodium thiosulfate, stearyl alcohol, and xanthan gum.

CLINICAL PHARMACOLOGY

The most widely accepted mechanism of action of sulfonamides in the Woods-Fildes theory which is based on the fact that sulfonamides act as competitive antagonists to para-aminobenzoic acid (PABA), an essential component for bacterial growth. While absorption through intact skin has not been determined, Sodium Sulfacetamide is readily absorbed from the gastrointestinal tract when taken orally and excreted in the urine, largely unchanged. The biological half-life has variously been reported as 7 to 12.8 hours. The exact mode of action of sulfur in the treatment of acne is unknown, but it has been reported that it inhibits the growth of Propionibacterium acnes and the formation of free fatty acids.

INDICATIONS

Sodium Sulfacetamide 9% & Sulfur 4.5% Was is indicated in the topical control of acne vulgaris, acne rosacea and seborrheic dermatitis.

CONTRAINDICATIONS

Sodium Sulfacetamide 9% & Sulfur 4.5% Wash is contraindicated for use by patients having known hypersensitivity to sulfonamides, sulfur, or any other component of this preparation. Sodium Sulfacetamide 9% & Sulfur 4.5% Wash in not to be used by patients with kidney disease.

WARNINGS

Although rare, sensitivity to Sodium Sulfacetamide may occur. Therefore, caution and careful supervision should be observed when prescribing this drug for patients who may be prone to hypersensitivity to topical sulfonamides. Systemic toxic reactions such as agranulocytosis, acute hemolytic anemia, purpura hemorrhagica, drug fever, jaundice, and contact dermatitis indicate hypersensitivity to sulfonamides. Particular caution should be employed if areas of denuded or abraded skin are involved.

FOR EXTERNAL USE ONLY. Keep away from eyes. Keep out of reach of children. Keep container tightly closed.

PRECAUTIONS

General

If irritation develops, use of this product should be discontinued and appropriate therapy instituted. Patients should be very carefully observed for possible local irritation or sensitization during long-term therapy. The object of this therapy is to achieve desquamation without irritation, but Sodium Sulfacetamide and Sulfur can cause reddening and scaling of the epidermis. These side effects are not unusual in the treatment of acne vulgaris, but patients should be cautioned about the possibility.

Information for Patients

Avoid contact with eyes, eyelids, lips and mucous membranes. If accidental contact occurs, rinse with water. If excessive irritation develops, discontinue use and consult your physician.

Carcinogenesis, Mutagenesis and Impairment of Fertility

Long-term studies in animals have not been performed to evaluate carcinogenic potential.

Pregnancy

Category C

Animal reproduction studies have not been conducted with Sodium Sulfacetamide 9% & Sulfur 4.5% Wash. It is also not known whether Sodium Sulfactamide 9% & Sulfur 4.5% Wash can cause fetal harm when administered to a pregnant woman or can affect reproduction capacity. Sodium Sulfacetamide 9% & Sulfur 4.5% Wash is administered to a nursing woman.

Pediatric Use

Safety and effectiveness in children under the age of 12 has not been established.

ADVERSE REACTIONS

Although rare, sodium sulfacetamide may cause local irritation.

DOSAGE AND ADMINISTRATION

Apply Sodium Sulfacetamide 9% & Sulfur 4.5% Wash once or twice daily to affected areas or as directed by your physician. Wet skin and liberally apply to areas to be cleansed. Massage gently into skin for 10-20 seconds, working into a lather. Rinse thoroughly and pat dry. If drying occurs, it may be controlled by rinsing off Sodium Sulfacetamide 9% & Sulfur 4.5% Wash sooner or using less often.

HOW SUPPLIED

Sodium Sulfacetamide 9% & Sulfur 4.5% Wash is available in a 16 oz (454 g) bottle, NDC 82429-301-21.

STORAGE

Store at 20°C to 25°C (68°F to 77°F), excursions permitted between 15°C and 30°C (between 59°F and 86°F). Brief exposure to temperatures up to 40°C (104°F) may be tolerated provided the mean kinetic temperature does not exceed 25°C (77°F), however such exposure should be minimized. Protect from freezing.

KEEP THIS AND ALL MEDICATION OUT OF THE REACH OF CHILDREN

Manufactured by:

Gabar Health Sciences, Corp.
Atlanta, Georgia 30354

PRINCIPAL DISPLAY PANEL - 454 g Bottle Label

NDC 82429-301-21

Rx only

For topical use only

Not ophthalmic use

Sodium Sulfacetamide 9% & Sulfur 4.5% Wash

Gabar Health Sciences Corp.

Net WT. 16oz. (454 g)